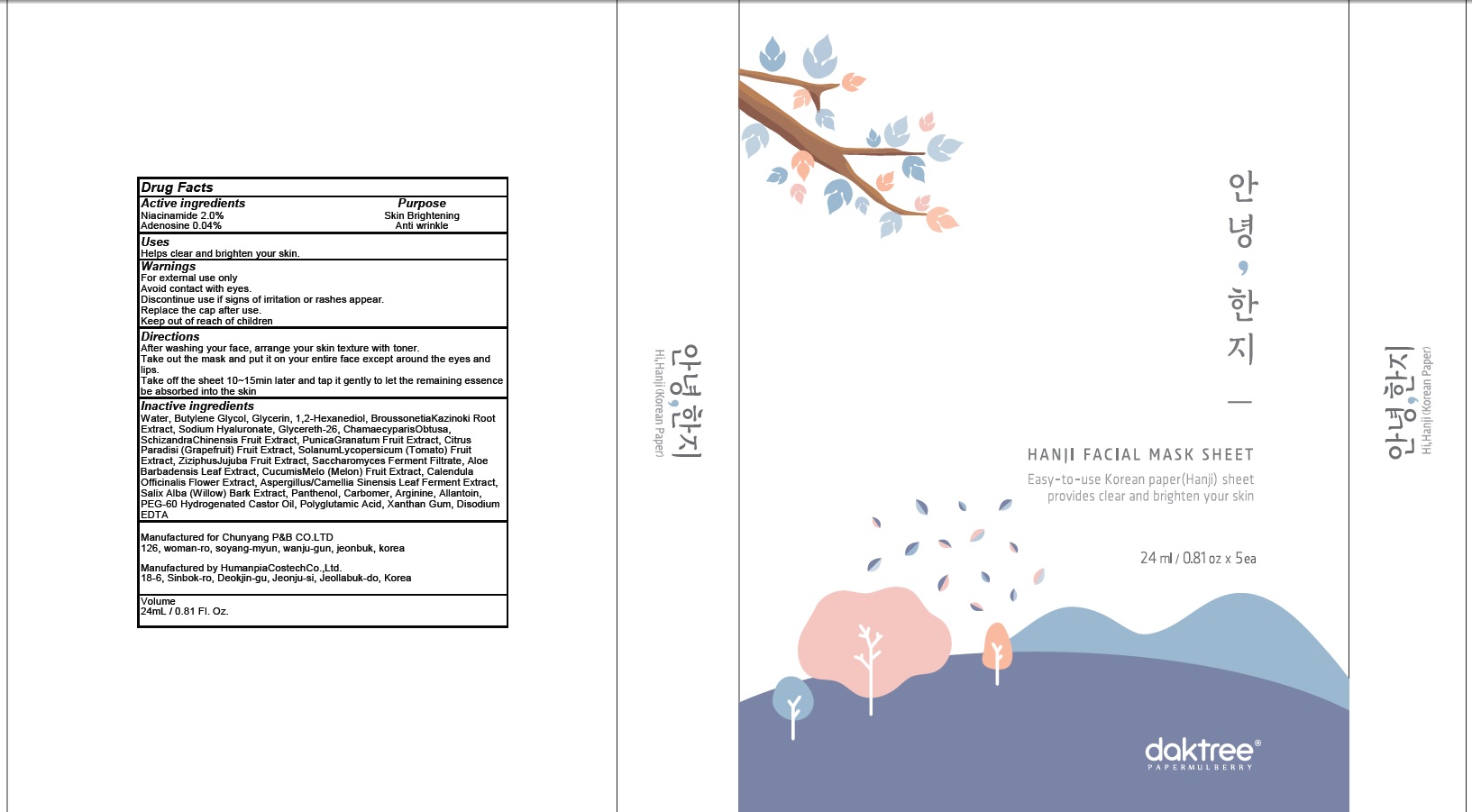 DRUG LABEL: HI HANJI
NDC: 73066-010 | Form: PATCH
Manufacturer: CHUNYANGP&B Co.,LTD
Category: otc | Type: HUMAN OTC DRUG LABEL
Date: 20190430

ACTIVE INGREDIENTS: Niacinamide 0.48 g/24 mL; Adenosine 0.009 g/24 mL
INACTIVE INGREDIENTS: Water; Butylene Glycol

ACTIVE INGREDIENT

Active ingredients: Niacinamide 2.0%, Adenosine 0.04%

INACTIVE INGREDIENT

Inactive ingredients:

Water, Butylene Glycol, Glycerin, 1,2-Hexanediol, Broussonetia Kazinoki Root Extract, Sodium Hyaluronate, Glycereth-26, Chamaecyparis Obtusa, Schizandra Chinensis Fruit Extract, Punica Granatum Fruit Extract, Citrus Paradisi (Grapefruit) Fruit Extract, Solanum Lycopersicum (Tomato) Fruit Extract, Ziziphus Jujuba Fruit Extract, Saccharomyces Ferment Filtrate, Aloe Barbadensis Leaf Extract, Cucumis Melo (Melon) Fruit Extract, Calendula Officinalis Flower Extract, Aspergillus/Camellia Sinensis Leaf Ferment Extract,
Salix Alba (Willow) Bark Extract, Panthenol, Carbomer, Arginine, Allantoin, PEG-60 Hydrogenated Castor Oil, Polyglutamic Acid, Xanthan Gum, Disodium EDTA

PURPOSE

Purpose: Skin Brightening, Anti wrinkle

WARNINGS

For external use only
Avoid contact with eyes.
Discontinue use if signs of irritation or rashes appear.
Replace the cap after use.
Keep out of reach of children

KEEP OUT OF REACH OF CHILDREN

Uses

Helps clear and brighten your skin.

Directions

After washing your face, arrange your skin texture with toner.
Take out the mask and put it on your entire face except around the eyes and lips.
Take off the sheet 10~15min later and tap it gently to let the remaining essence be absorbed into the skin